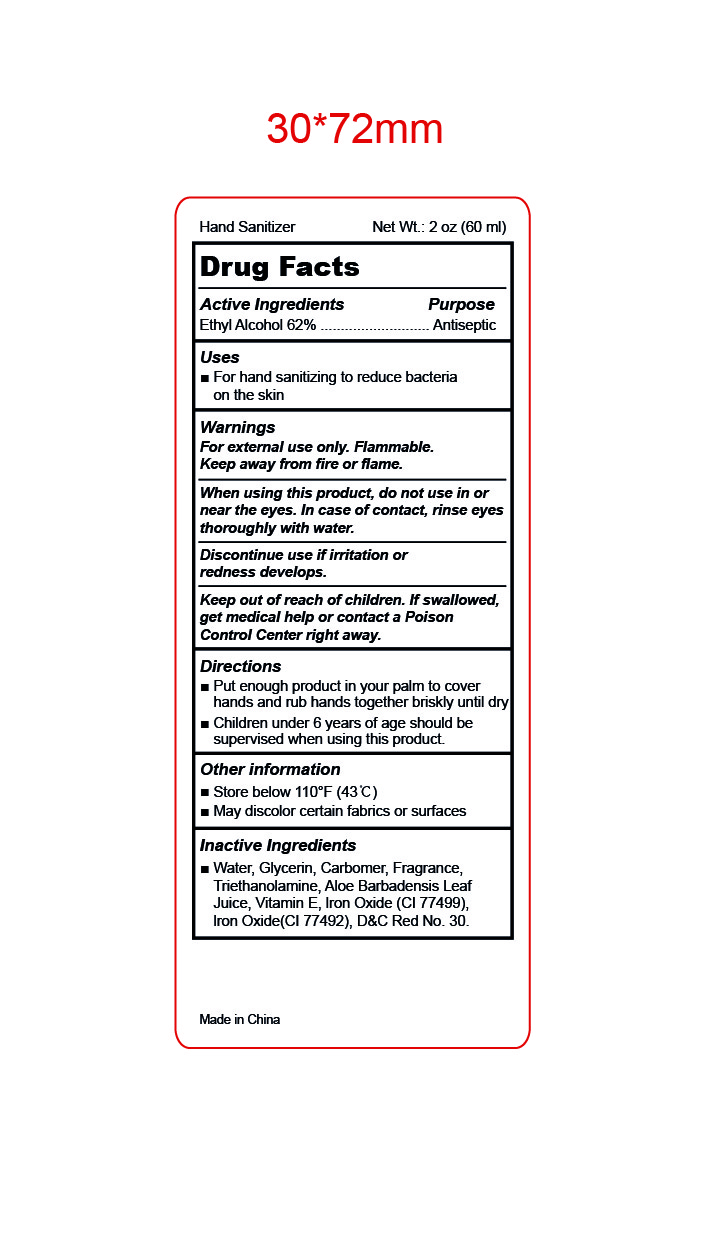 DRUG LABEL: Hand Sanitizer
NDC: 87001-003 | Form: GEL
Manufacturer: HAIAN KANGRUI TEXTILE CO., LTD.
Category: otc | Type: HUMAN OTC DRUG LABEL
Date: 20250812

ACTIVE INGREDIENTS: ALCOHOL 62 g/112 mL
INACTIVE INGREDIENTS: ALOE VERA LEAF; .ALPHA.-TOCOPHEROL; FERRIC OXIDE YELLOW; FERROSOFERRIC OXIDE; D&C RED NO. 30; GLYCERIN; WATER; CARBOMER INTERPOLYMER TYPE B (ALLYL PENTAERYTHRITOL CROSSLINKED); TROLAMINE

87001-003

Active Ingredient

Ethyl Alcohol 62%

Purpose

Antiseptic

Uses

For hand sanitizing to reduce bacteria on the skin.

Warnings

For external use only.

Flammable. Keep away from fire and flame.

When using this product，

do not use in or near the eyes.In case of contact，rinse eyes thoroughly with water.

Discontinue use

if irritation or redness develops.

Keep out of reach of children.

If swallowed, get medical help or contact a Poison Control Center right away.

Directions

Put enough product in your palm to cover hands and rub hands together briskly until dry.

Children under 6 years of age should be supervised when using this product.

Other information

Store Below 110℉ (43℃)
May discolor certain fabrocs or surfaces

Inactive ingredients

Water, Glycerin, Carbomer, Fragrance, Triethanolamine, Aloe Barbadensis Leaf Juice, Vitamin E, Iron Oxide(CI 77499), Iron Oxide(CI 77492), D&C Red No. 30